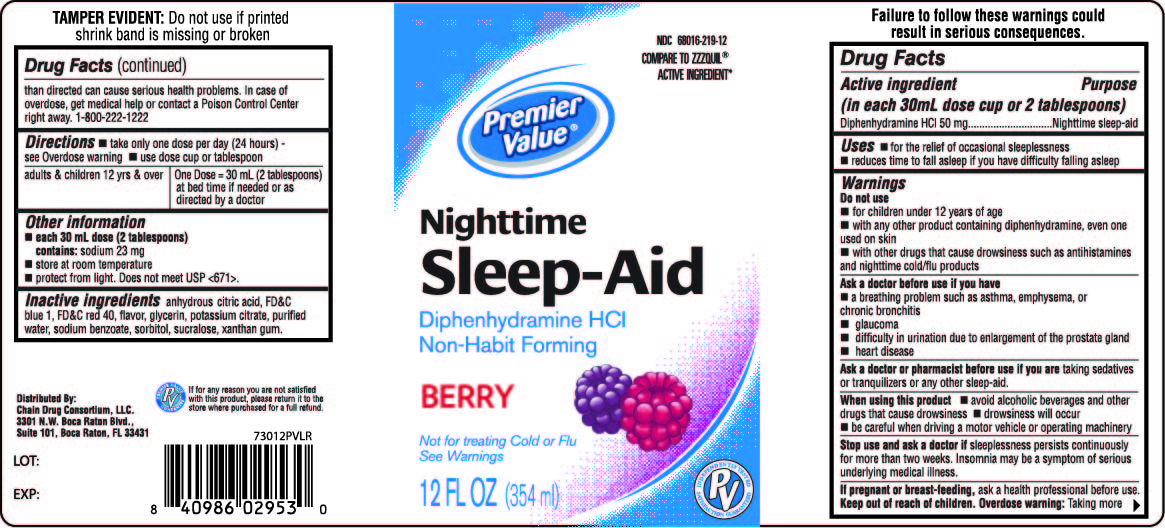 DRUG LABEL: Premier Value Nighttime Sleep-Aid Liquid
NDC: 68016-219 | Form: LIQUID
Manufacturer: Chain Drug Consortium
Category: otc | Type: HUMAN OTC DRUG LABEL
Date: 20241028

ACTIVE INGREDIENTS: DIPHENHYDRAMINE HYDROCHLORIDE 50 mg/30 mL
INACTIVE INGREDIENTS: CITRIC ACID MONOHYDRATE; FD&C BLUE NO. 1; FD&C RED NO. 40; GLYCERIN; POTASSIUM CITRATE; WATER; SODIUM BENZOATE; SORBITOL; SUCRALOSE; XANTHAN GUM

Premier Value Nighttime Sleep-Aid

Drug Facts

Active ingredients (in each 30 mL dose cup or 2 tablespoons)

Diphenhydramine HCl 50 mg

Purpose

Nighttime sleep-aid

Uses

- for the relief of occasional sleeplessness
- reduces time to fall asleep if you have difficulty falling asleep

Warnings

Do not use

- for children under 12 years of age
- with any other product containing diphenhydramine, even one used on skin
- with other drugs that cause drowsiness such as antihistamines and nighttime cold/flu products

Ask a doctor before use if you have

- a breathing problem such as asthma, emphysema, or chronic bronchitis
- glaucoma
- difficulty in urination due to enlargement of the prostate gland
- heart disease

Ask a doctor or pharmacist before use if you are taking sedatives or tranquilizers or any other sleep aid

When using this product

- avoid alcoholic beverages and other drugs that cause drowsiness
- drowsiness will occur
- be careful when driving a motor vehicle or operating machinery

Stop use and ask a doctor if sleeplessness persists continuously for more than 2 weeks. Insomnia may be a symptom of serious underlying medical illness.

PREGNANCY OR BREAST FEEDING

If pregnant or breast-feeding, ask a health professional before use.

Keep out of reach of children.

Overdose warning

Taking more than directed can cause serious health problems. In case of overdose, get medical help or contact a Poison Control Center right away.

Directions

- take only one dose per day (24 hours) - see Overdose warning
- use dose cup or tablespoon

adults & children 12 yrs & over | One Dose = 30 mL (2 tablespoons) at bed time if needed or as directed by a doctor

Other information

- each 30 mL dose (2 tablespoons) contains: sodium 23 mg
- store at room temperature
- protect from light. Does not meet USP <671>.

Inactive ingredients

anhydrous citric acid, carboxymethylcelluose sodium, FD&C blue 1, FD&C red 40, flavor, glycerin, potassium citrate, purified water, sodium benzoate, sorbitol, sucralose.

Failure to follow these warnings could result in serious consequences

TAMPER EVIDENT: This package is safety sealed & child resistant. Use only if blisters are intact. If difficult to open, use scissors.

This product is not manufactured or distributed by Procter & Gamble, the distributor of ZzzQuil™.

Distributed by:

Chain Drug Consortium LLC.

3301 N.W. Boca Raton Blvd.

Suite 101, Boca Raton FL 33431

PRINCIPAL DISPLAY PANEL - 354 ml Bottle Label

Premier Value
Nighttime

Sleep-Aid

Diphenhydramine HCl /

- Non-Habit Forming

Berry Flavor

Not for treating Cold or Flu
See Warnings

12 FL OZ (354 ml)